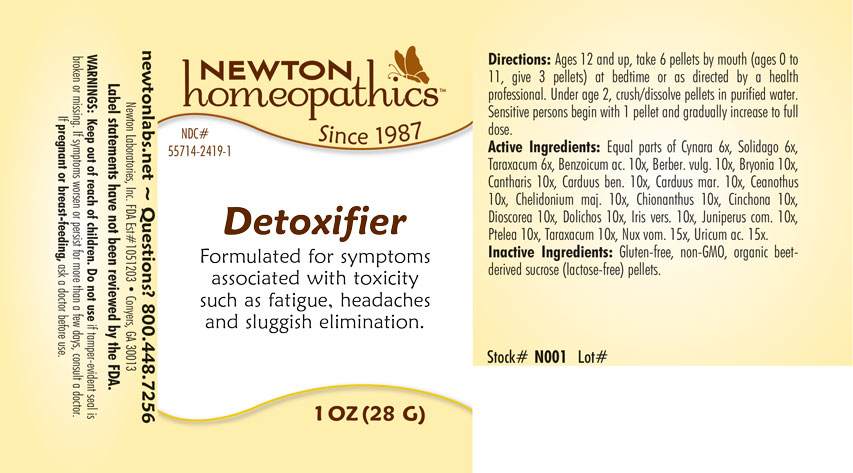 DRUG LABEL: Detoxifier
NDC: 55714-2419 | Form: PELLET
Manufacturer: Newton Laboratories, Inc.
Category: homeopathic | Type: HUMAN OTC DRUG LABEL
Date: 20201124

ACTIVE INGREDIENTS: BENZOIC ACID 10 [hp_X]/1 g; BERBERIS VULGARIS ROOT BARK 10 [hp_X]/1 g; BRYONIA ALBA ROOT 10 [hp_X]/1 g; LYTTA VESICATORIA 10 [hp_X]/1 g; CENTAUREA BENEDICTA 10 [hp_X]/1 g; CEANOTHUS AMERICANUS LEAF 10 [hp_X]/1 g; CHELIDONIUM MAJUS 10 [hp_X]/1 g; CHIONANTHUS VIRGINICUS BARK 10 [hp_X]/1 g; CINCHONA OFFICINALIS BARK 10 [hp_X]/1 g; DIOSCOREA VILLOSA TUBER 10 [hp_X]/1 g; MUCUNA PRURIENS FRUIT TRICHOME 10 [hp_X]/1 g; IRIS VERSICOLOR ROOT 10 [hp_X]/1 g; JUNIPER BERRY 10 [hp_X]/1 g; STRYCHNOS NUX-VOMICA SEED 15 [hp_X]/1 g; PTELEA TRIFOLIATA BARK 10 [hp_X]/1 g; TARAXACUM OFFICINALE 10 [hp_X]/1 g; SILYBUM MARIANUM SEED 10 [hp_X]/1 g; CYNARA SCOLYMUS LEAF 6 [hp_X]/1 g; SOLIDAGO VIRGAUREA FLOWERING TOP 6 [hp_X]/1 g; URIC ACID 15 [hp_X]/1 g
INACTIVE INGREDIENTS: SUCROSE

Detox 2419P

INDICATIONS & USAGE SECTION

Formulated for symptoms associated with toxicity such as fatigue, headaches and sluggish elimination.

DOSAGE & ADMINISTRATION SECTION

Directions: Ages 12 and up, take 6 pellets by mouth (ages 0 to 11, give 3 pellets) at bedtime or as directed by a health professional. Under age 2, crush or dissolve pelles in pirified water. Sensitive persons begin with 1 pellet and gradually increase to full dose.

OTC - ACTIVE INGREDIENT SECTION

Equal parts of Cynara 6x, Solidago 6x, Taraxacum 6x, Benzoicum ac. 10x, Berber. vulg. 10x, Bryonia 10x, Cantharis 10x, Carduus ben. 10x, Carduus mar. 10x, Ceanothus 10x, Chelidonium maj. 10x, Chionanthus 10x, Cinchona 10x, Dioscorea 10x, Dolichos 10x, Iris vers. 10x, Juniperus com. 10x, Ptelea 10x, Taraxacum 10x, Nux vom. 15, Uricum ac. 15x.

OTC - PURPOSE SECTION

Formulated for symptoms associated with toxicity such as fatigue, headaches and sluggish elimination.

INACTIVE INGREDIENT SECTION

Inactive Ingredients: Gluten-free, non-GMO, beet-derived sucrose (lactose-free) pellets.

QUESTIONS SECTION

newtonlabs.net - Questions ? 800.448.7256

Newton Laboratories, Inc. FDA Est # 1051203 - Conyers, GA 30013

WARNINGS SECTION

WARNINGS: Keep out of reach of children. Do not use if tamper-evident seal is broken or missing. If symptoms worsen or persist for more than a few days, consult a doctor. If pregnant or breast-feeding, ask a doctor before use.

OTC - PREGNANCY OR BREAST FEEDING SECTION

If pregnant or breast-feeding, ask a doctor before use.

OTC - KEEP OUT OF REACH OF CHILDREN SECTION

Keep out of reach of children.